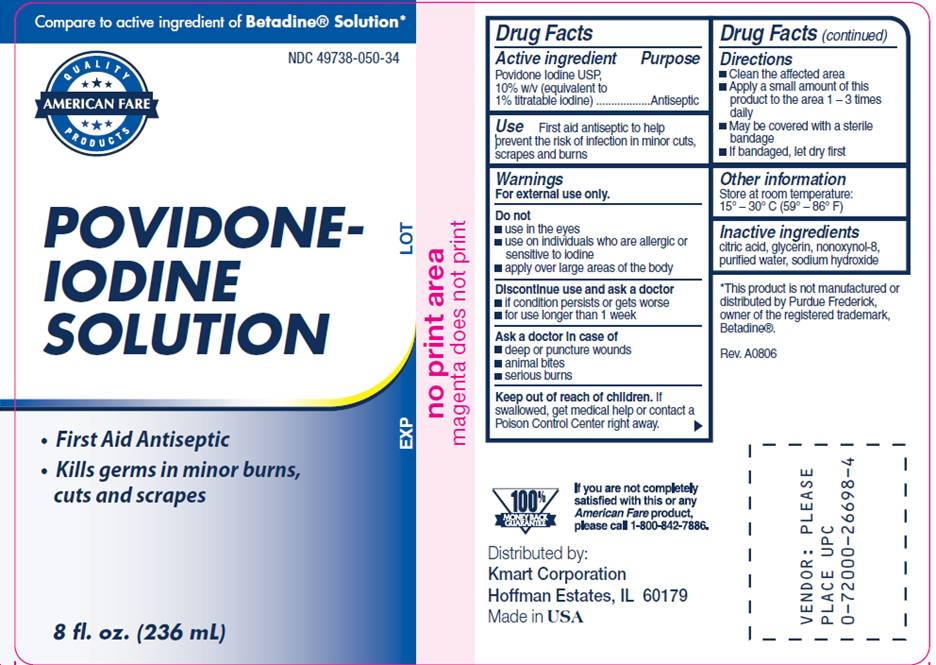 DRUG LABEL: Povidone Iodine
NDC: 49738-050 | Form: SOLUTION
Manufacturer: Kmart Corporation
Category: otc | Type: HUMAN OTC DRUG LABEL
Date: 20100415

ACTIVE INGREDIENTS: povidone-iodine .10 mg/1 mL
INACTIVE INGREDIENTS: citric acid monohydrate; glycerin; sodium hydroxide; water

DRUG FACTS

ACTIVE INGREDIENT

Povidone Iodine USP, 10% w/v (equivalent to 1% titratable iodine)

PURPOSE

Antiseptic

USE

First aid antiseptic to help prevent the risk of infection in minor cuts, scrapes and burns

WARNINGS

For external use only.

Do not

- use in the eyes
- use on individuals who are allergic or sensitive to iodine
- apply over large areas of the body

Discontinue use and ask a doctor

- if condition persists or gets worse
- for use longer than 1 week

Ask a doctor in case of

- deep or puncture wounds
- animal bites
- serious burns

Keep out of reach of children

If swallowed, get medical help or contact a Poison Control Center right away.

DIRECTIONS

- Clean the affected area
- Apply a small amount of this product to the area 1-3 times daily
- May be covered with a sterile bandage
- If bandaged, let dry first

OTHER INFORMATION

Store at room temperature 15° - 30° C (59° - 86° F)

INACTIVE INGREDIENTS

citric acid, glycerin, nonoxynol-8, purified water, sodium hydroxide

LABEL INFORMATION

Compare to active ingredient of Betadine® Solution*

NDC 49738-050-34

AMERICAN FARE

POVIDONE-
IODINE
SOLUTION

- First Aid Antiseptic
- Kills germs in minor burns, cuts and scrapes

8 fl. oz. (236 mL)

*This product is not manufactured of distributed by Purdue Frederick, owner of the registered trademark, Betadine®.

If you are not completely satisfied with this or any American Fare product, please call 1-800-842-7886.

Distributed by:
Kmart Corporation
Hoffman Estates, IL 60179
Made in USA